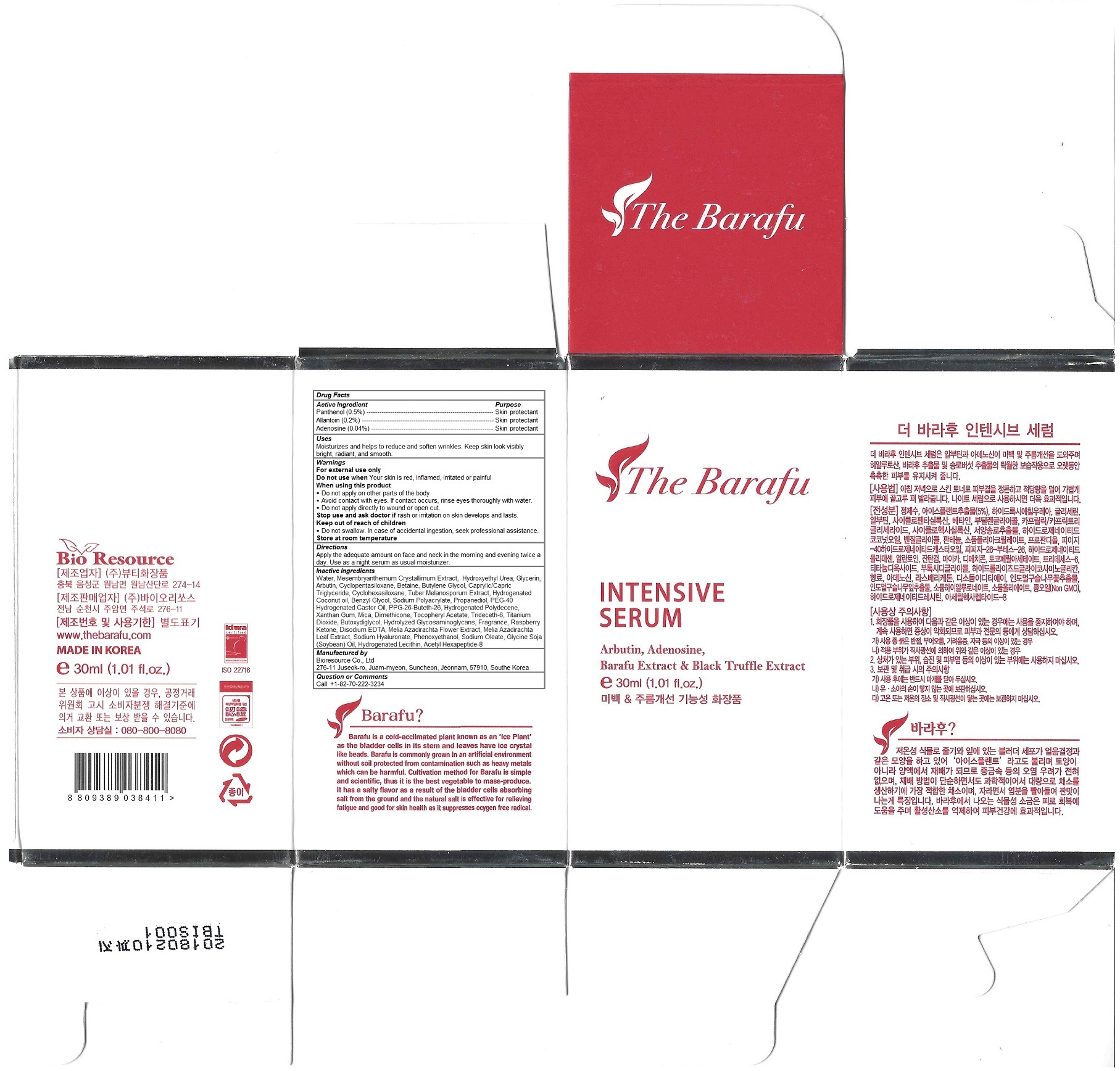 DRUG LABEL: The Barafu Intensive Serum
NDC: 71099-100 | Form: LIQUID
Manufacturer: Bioresource Co., Ltd
Category: otc | Type: HUMAN OTC DRUG LABEL
Date: 20161205

ACTIVE INGREDIENTS: Panthenol 0.15 g/30 mL; ALLANTOIN 0.06 g/30 mL; ADENOSINE 0.012 g/30 mL
INACTIVE INGREDIENTS: WATER; MESEMBRYANTHEMUM CRYSTALLINUM WHOLE; HYDROXYETHYL UREA; Glycerin; Arbutin; CYCLOMETHICONE 5; Betaine; Butylene Glycol; MEDIUM-CHAIN TRIGLYCERIDES; CYCLOMETHICONE 6; BLACK TRUFFLE; HYDROGENATED COCONUT OIL; ETHYLENE GLYCOL MONOBENZYL ETHER; SODIUM POLYACRYLATE (2500000 MW); Propanediol; POLYOXYL 40 HYDROGENATED CASTOR OIL; PPG-26-BUTETH-26; HYDROGENATED POLYDECENE (550 MW); Xanthan Gum; Mica; Dimethicone; .ALPHA.-TOCOPHEROL ACETATE; Trideceth-6; Titanium Dioxide; DIETHYLENE GLYCOL MONOBUTYL ETHER; HYDROLYZED GLYCOSAMINOGLYCANS (BOVINE; 50000 MW); 4-(P-HYDROXYPHENYL)-2-BUTANONE; EDETATE DISODIUM ANHYDROUS; AZADIRACHTA INDICA FLOWER; AZADIRACHTA INDICA LEAF; HYALURONATE SODIUM; PHENOXYETHANOL; SODIUM OLEATE; SOYBEAN OIL; HYDROGENATED SOYBEAN LECITHIN; Acetyl Hexapeptide-8

The Barafu Intensive Serum

Active Ingredients

Panthenol (0.5%)
Allantoin (0.2%)
Adenosine (0.04%)

Purpose

skin protectant

Keep out of reach of children

 Do not swallow. In case of accidental ingestion, seek professional assistance.

Warnings

For external use only
Do not use when Your skin is red, inflamed, irritated or painful
When using this product
 Do not apply on other parts of the body
 Avoid contact with eyes. If contact occurs, rinse eyes thoroughly with water.
 Do not apply directly to wound or open cut.
Stop use and ask doctor if rash or irritation on skin develops and lasts.

Store at room temperature

Uses

Moisturizes and helps to reduce and soften wrinkles. Keep skin look visibly bright, radiant, and smooth.

Directions

Apply the adequate amount on face and neck in the morning and evening twice a day. Use as a night serum as usual moisturizer.

Inactive Ingredients

Water, Mesembryanthemum Crystallimum Extract, Hydroxyethyl Urea, Glycerin, Arbutin, Cyclopentasiloxane, Betaine, Butylene Glycol, Caprylic/Capric Triglyceride, Cyclohexasiloxane, Tuber Melanosporum Extract, Hydrogenated Coconut oil, Benzyl Glycol, Sodium Polyacrylate, Propanediol, PEG-40 Hydrogenated Castor Oil, PPG-26-Buteth-26, Hydrogenated Polydecene, Xanthan Gum, Mica, Dimethicone, Tocopheryl Acetate, Trideceth-6, Titanium Dioxide, Butoxydiglycol, Hydrolyzed Glycosaminoglycans, Fragrance, Raspberry Ketone, Disodium EDTA, Melia Azadirachta Flower Extract, Melia Azadirachta Leaf Extract, Sodium Hyaluronate, Phenoxyethanol, Sodium Oleate, Glycine Soja (Soybean) Oil, Hydrogenated Lecithin, Acetyl Hexapeptide-8